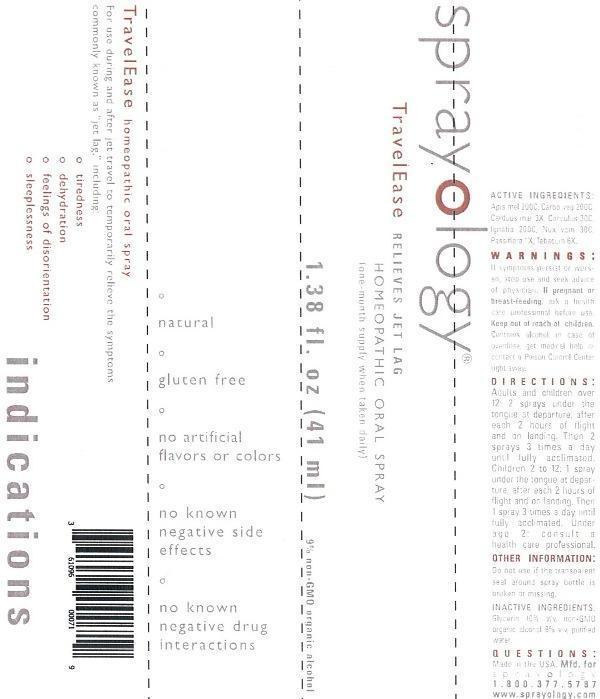 DRUG LABEL: Sprayology TravelEase
NDC: 61096-0007 | Form: LIQUID
Manufacturer: Eight and Company
Category: homeopathic | Type: HUMAN OTC DRUG LABEL
Date: 20140122

ACTIVE INGREDIENTS: APIS MELLIFERA 200 [hp_C]/41 mL; ACTIVATED CHARCOAL 200 [hp_C]/41 mL; SILYBUM MARIANUM SEED 3 [hp_X]/41 mL; ANAMIRTA COCCULUS SEED 30 [hp_C]/41 mL; STRYCHNOS IGNATII SEED 200 [hp_C]/41 mL; STRYCHNOS NUX-VOMICA SEED 30 [hp_C]/41 mL; PASSIFLORA INCARNATA FLOWERING TOP 1 [hp_X]/41 mL; TOBACCO LEAF 6 [hp_X]/41 mL
INACTIVE INGREDIENTS: GLYCERIN; ALCOHOL; WATER

Sprayology TravelEase

ACTIVE INGREDIENT

Active Ingredients: Apis mellifica 200C, Carbo vegetabilis 200C, Carduus marianus 3X, Cocculus Indicus 30C, Ignatia amara 200C, Nux vomica 30C, Passiflora incarnata 1X, Tabacum 6X.

WARNINGS

Warnings: If symptoms persist or worsen, stop use and seek advice of physician. If pregnant or breast-feeding, ask a health care professional before use. Keep out of reach of children. Contains alcohol, in case of overdose, get medical help or contact a Poison Control Center right away.

Keep out of reach of children.

PURPOSE

For use during and after jet travel to temporarily relieve the symptoms commonly known as "jet lag", including:

- tiredness
- dehydration
- feeling of disorientation
- sleeplessness

Directions:

- Adults and children over 12: 2 sprays under the tongue at departure, after each 2 hours of flight and on landing. Then 2 sprays 3 times a day until fully acclimated.
- Children 2 to 12: 1 spray under tongue at departure, after each 2 hours of flight and on landing. Then 1 spray 3 times a day until fully acclimated.
- Under age 2: consult a health care professional.

Other Information: Do not use if the transparent seal around spray bottle is broken or missing.

INACTIVE INGREDIENT

Inactive Ingredients: Glycerin 10%, v/v, non-GMO organic alcohol 9% v/v, purified water.

INDICATIONS AND USAGE

For use during and after jet travel to temporarily relieve the symptoms commonly known as "jet lag", including:

° tiredness

° dehydration

° feeling of disorientation

° sleeplessness

° natural

° gluten free

° no artificial flavors or colors

° no known negative side effects

° no known negative drug interactions